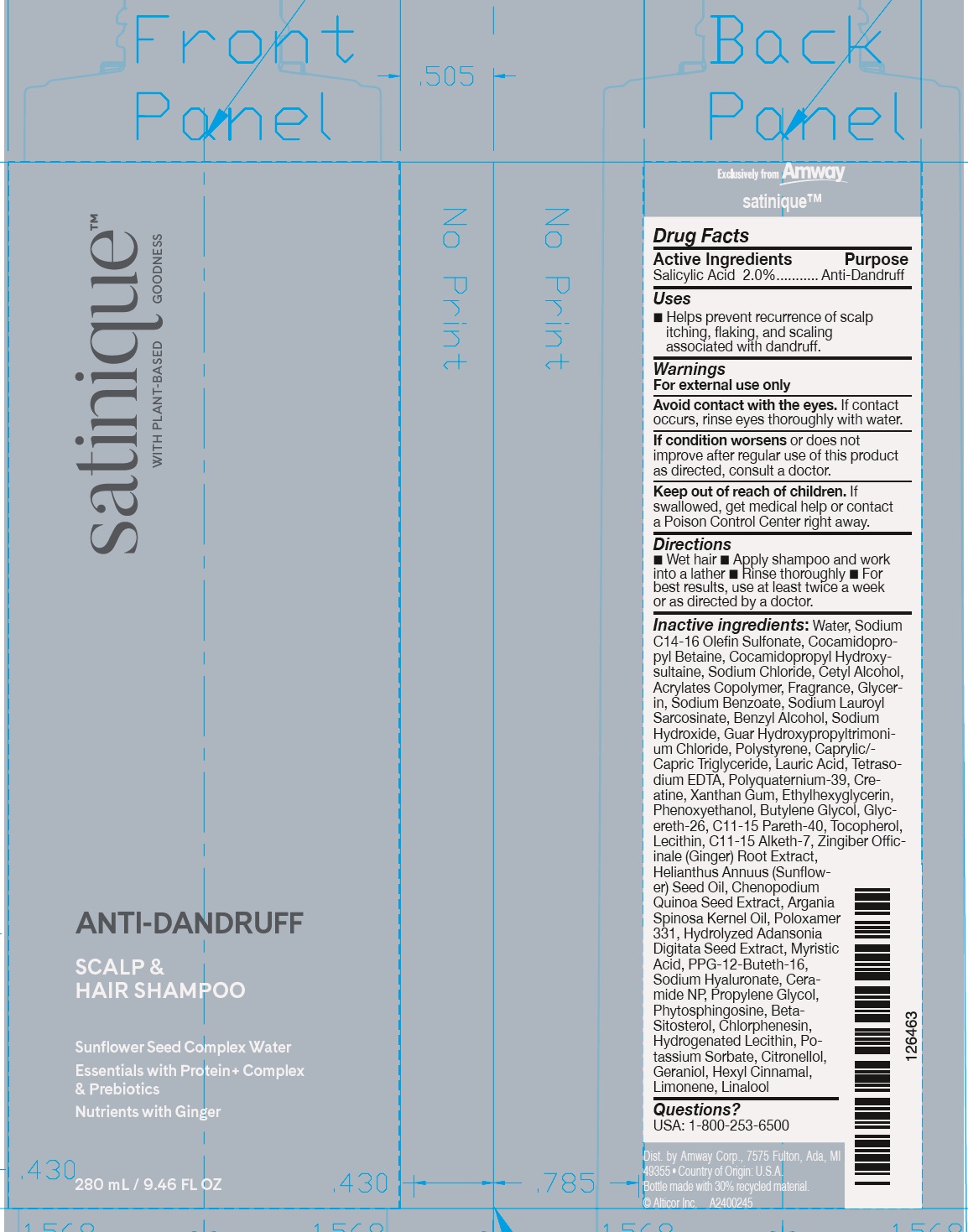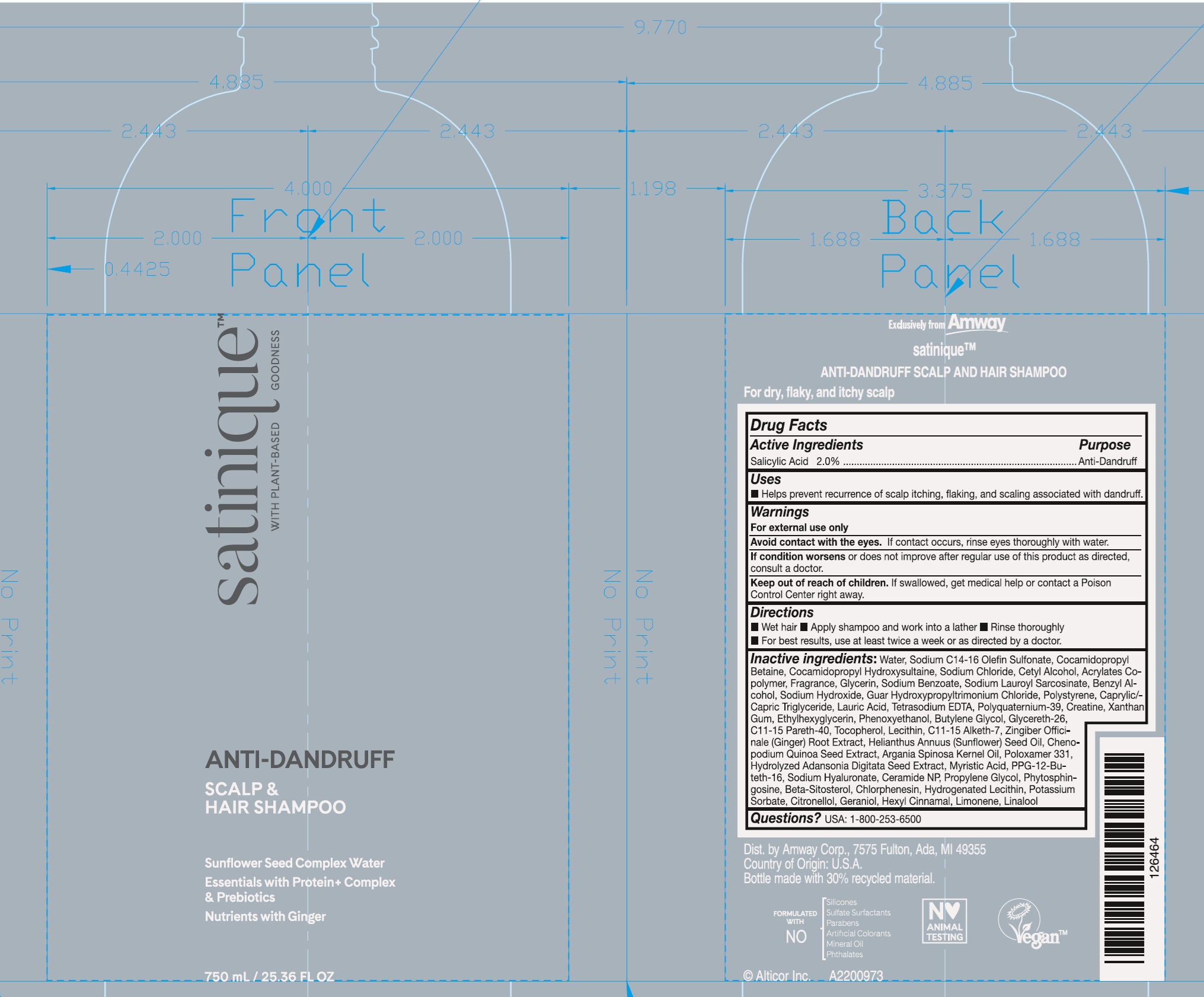 DRUG LABEL: Satinique Anti Dandruff Scalp and Hair
NDC: 10056-536 | Form: LIQUID
Manufacturer: Access Business Group LLC
Category: otc | Type: HUMAN OTC DRUG LABEL
Date: 20241209

ACTIVE INGREDIENTS: SALICYLIC ACID 20 mg/1 mL
INACTIVE INGREDIENTS: WATER; SODIUM C14-16 OLEFIN SULFONATE; COCAMIDOPROPYL BETAINE; COCAMIDOPROPYL HYDROXYSULTAINE; SODIUM CHLORIDE; CETYL ALCOHOL; GLYCERIN; SODIUM BENZOATE; SODIUM LAUROYL SARCOSINATE; BENZYL ALCOHOL; SODIUM HYDROXIDE; GUAR HYDROXYPROPYLTRIMONIUM CHLORIDE; MEDIUM-CHAIN TRIGLYCERIDES; LAURIC ACID; EDETATE SODIUM; CREATINE; XANTHAN GUM; ETHYLHEXYLGLYCERIN; PHENOXYETHANOL; BUTYLENE GLYCOL; GLYCERETH-26; C11-15 PARETH-40; TOCOPHEROL; C11-15 ALKETH-7; GINGER; SUNFLOWER OIL; CHENOPODIUM QUINOA SEED; ARGAN OIL; POLOXAMER 331; MYRISTIC ACID; PPG-12-BUTETH-16; HYALURONATE SODIUM; CERAMIDE NP; PROPYLENE GLYCOL; PHYTOSPHINGOSINE; .BETA.-SITOSTEROL; CHLORPHENESIN; POTASSIUM SORBATE; .BETA.-CITRONELLOL, (R)-; GERANIOL; .ALPHA.-HEXYLCINNAMALDEHYDE; LIMONENE, (+)-; LINALOOL, (+/-)-

Satinique Anti Dandruff Scalp and Hair Shampoo

Active Ingredients

Salicylic Acid 2.0%

Purpose

Anti-Dandruff

Uses

- Helps prevent recurrence of scalp itching, flaking, and scaling associated with dandruff.

Warnings

For external use only

Avoid contact with the eyes. If contact occurs, rinse eyes thoroughly with water.

If condition worsensor does not improve after regular use of this product as directed, consult a doctor.

Keep out of reach of children.

If swallowed, get medical help or contact a Poison Control Center right away.

Directions

- Wet hair
- Apply shampoo and work into a lather
- Rinse thoroughly
- For best results, use at least twice a week or as directed by a doctor.

Inactive ingredients:

Water, Sodium C14-16 Olefin Sulfonate, Cocamidopropyl Betaine, Cocamidopropyl Hydroxysultaine, Sodium Chloride, Cetyl Alcohol, Acrylates Copolymer, Fragrance, Glycerin, Sodium Benzoate, Sodium Lauroyl Sarcosinate, Benzyl Alcohol, Sodium Hydroxide, Guar Hydroxypropyltrimonium Chloride, Polystyrene, Caprylic/-Capric Triglyceride, Lauric Acid, Tetrasodium EDTA, Polyquaternium-39, Creatine, Xanthan Gum, Ethylhexyglycerin, Phenoxyethanol, Butylene Glycol, Glycereth- 26, C11-15 Pareth-40, Tocopherol, Lecithin, C11-15 Alketh-7, Zingiber Officinale (Ginger) Root Extract, Helianthus Annuus (Sunflower) Seed Oil, Chenopodium Quinoa Seed Extract, Argania Spinosa Kernel Oil, Poloxamer 331, Hydrolyzed Adansonia Digitata Seed Extract, Myristic Acid, PPG-12-Buteth-16, Sodium Hyaluronate, Ceramide NP, Propylene Glycol, Phytosphingosine, Beta- Sitosterol, Chlorphenesin, Hydrogenated Lecithin, Potassium Sorbate, Citronellol, Geraniol, Hexyl Cinnamal, Limonene, Linalool

Questions?

USA: 1-800-253-6500